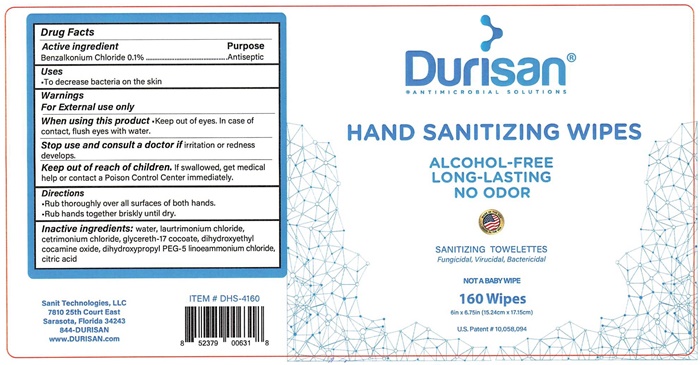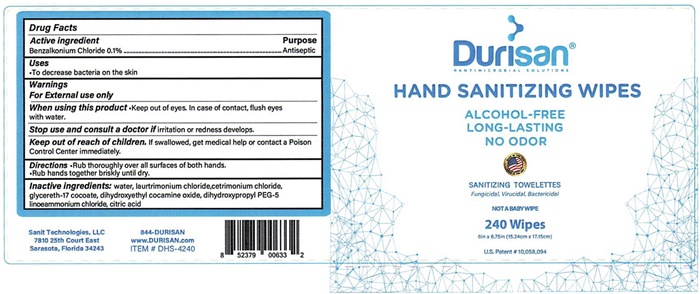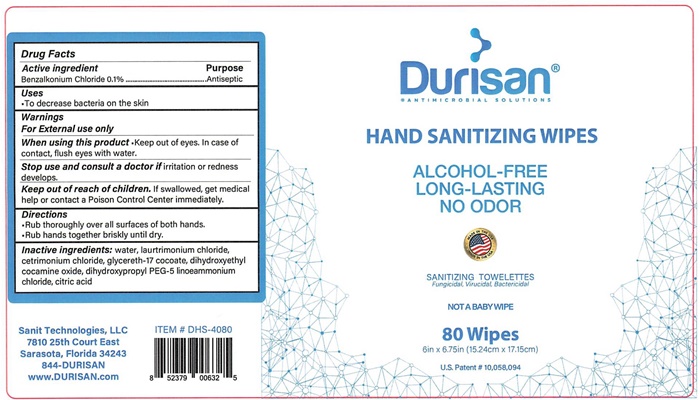 DRUG LABEL: Hand Sanitizing Wipes
NDC: 71120-613 | Form: LIQUID
Manufacturer: Sanit Technologies LLC
Category: otc | Type: HUMAN OTC DRUG LABEL
Date: 20200307

ACTIVE INGREDIENTS: BENZALKONIUM CHLORIDE 2.5 mg/250 mL
INACTIVE INGREDIENTS: WATER; LAURTRIMONIUM CHLORIDE; GLYCERETH-17 COCOATE; DIHYDROXYETHYL COCAMINE OXIDE; DIHYDROXYPROPYL PEG-5 LINOLEAMMONIUM CHLORIDE; CITRIC ACID ACETATE

Durisan Hand Sanitizing Wipes - 613

Active Ingredient

Benzalkonium Chloride 0.1%

Purpose

Antiseptic

Uses

- To decrease bacteria on the skin

Warnings

For External use only

When using this product • Keep out of eyes. In case of contact, flush eyes with water.

Stop Use

Stop use and consult a doctor if irritation or redness develops

Keep out of reach of children. If swallowed, get medical help or contact a Poison Control Center immediately.

Dosage and Administration

- Rub thoroughly over all surfaces of both hands.
- Rub hands together briskly until dry.

Inactive Ingredients

Inactive ingredients: water, laurtrimonium chloride, cetrimonium chloride, glycereth-17 cocoate, dihydroxyethyl cocamine oxide, dihydroxypropyl PEG-5, linoeammonium chloride, citric acid

Durisan Hand Sanitizing Wipes

Drug Facts; Active Ingredient Purpose; Benzalkonium Chloride 0.1% ………….…. Antiseptic; Uses; - To decrease bacteria on the skin; Warnings; For External use only; When using this product • Keep out of eyes. In case of contact, flush eyes with water.; Stop use and consult a doctor if irritation or redness develops.; Keep out of reach of children. If swallowed, get medical help or contact a Poison Control Center immediately.; Directions; - Rub thoroughly over all surfaces of both hands. - Rub hands together briskly until dry.; Inactive ingredients: water, laurtrimonium chloride, cetrimonium chloride, glycereth-17 cocoate, dihydroxyethyl cocamine oxide, dihydroxypropyl PEG-5, linoeammonium chloride, citric acid |  | Durisan ®; - ANTIMICROBIAL SOLUTIONS; HAND SANITIZING WIPES; ALCOHOL-FREE; LONG-LASTING; NO ODOR; SANITIZING TOWELETTES; Fungicidal, Viricidal, Bactericidal; NOT A BABY WIPE; 80 Wipes; 6in x 6.75in (15.24cm x 17.15cm); U.S. Patent # 10,058,094
Sanit Technologies, LLC; 7810 25th Court East; Sarasota, Florida 34243; 844-DURISAN; www.DURISAN.com | ITEM # DHS-4080; 8 52379 00632 5 | Durisan ®; - ANTIMICROBIAL SOLUTIONS; HAND SANITIZING WIPES; ALCOHOL-FREE; LONG-LASTING; NO ODOR; SANITIZING TOWELETTES; Fungicidal, Viricidal, Bactericidal; NOT A BABY WIPE; 80 Wipes; 6in x 6.75in (15.24cm x 17.15cm); U.S. Patent # 10,058,094

Drug Facts; Active Ingredient Purpose; Benzalkonium Chloride 0.1% ………….…. Antiseptic; Uses; - To decrease bacteria on the skin; Warnings; For External use only; When using this product • Keep out of eyes. In case of contact, flush eyes with water.; Stop use and consult a doctor if irritation or redness develops.; Keep out of reach of children. If swallowed, get medical help or contact a Poison Control Center immediately.; Directions; - Rub thoroughly over all surfaces of both hands. - Rub hands together briskly until dry.; Inactive ingredients: water, laurtrimonium chloride, cetrimonium chloride, glycereth-17 cocoate, dihydroxyethyl cocamine oxide, dihydroxypropyl PEG-5, linoeammonium chloride, citric acid |  | Durisan ®; - ANTIMICROBIAL SOLUTIONS; HAND SANITIZING WIPES; ALCOHOL-FREE; LONG-LASTING; NO ODOR; SANITIZING TOWELETTES; Fungicidal, Viricidal, Bactericidal; NOT A BABY WIPE; 160 Wipes; 6in x 6.75in (15.24cm x 17.15cm); U.S. Patent # 10,058,094
Sanit Technologies, LLC; 7810 25th Court East; Sarasota, Florida 34243; 844-DURISAN; www.DURISAN.com | ITEM # DHS-4160; 8 52379 00631 8 | Durisan ®; - ANTIMICROBIAL SOLUTIONS; HAND SANITIZING WIPES; ALCOHOL-FREE; LONG-LASTING; NO ODOR; SANITIZING TOWELETTES; Fungicidal, Viricidal, Bactericidal; NOT A BABY WIPE; 160 Wipes; 6in x 6.75in (15.24cm x 17.15cm); U.S. Patent # 10,058,094

Drug Facts; Active Ingredient Purpose; Benzalkonium Chloride 0.1% ………….…. Antiseptic; Uses; - To decrease bacteria on the skin; Warnings; For External use only; When using this product • Keep out of eyes. In case of contact, flush eyes with water.; Stop use and consult a doctor if irritation or redness develops.; Keep out of reach of children. If swallowed, get medical help or contact a Poison Control Center immediately.; Directions; - Rub thoroughly over all surfaces of both hands. - Rub hands together briskly until dry.; Inactive ingredients: water, laurtrimonium chloride, cetrimonium chloride, glycereth-17 cocoate, dihydroxyethyl cocamine oxide, dihydroxypropyl PEG-5, linoeammonium chloride, citric acid |  |  | Durisan ®; - ANTIMICROBIAL SOLUTIONS; HAND SANITIZING WIPES; ALCOHOL-FREE; LONG-LASTING; NO ODOR; SANITIZING TOWELETTES; Fungicidal, Viricidal, Bactericidal; NOT A BABY WIPE; 240 Wipes; 6in x 6.75in (15.24cm x 17.15cm); U.S. Patent # 10,058,094
Sanit Technologies, LLC; 7810 25th Court East; Sarasota, Florida 34243 | 844-DURISAN; www.DURISAN.com; ITEM # DHS-4240 | 8 52379 00633 2 | Durisan ®; - ANTIMICROBIAL SOLUTIONS; HAND SANITIZING WIPES; ALCOHOL-FREE; LONG-LASTING; NO ODOR; SANITIZING TOWELETTES; Fungicidal, Viricidal, Bactericidal; NOT A BABY WIPE; 240 Wipes; 6in x 6.75in (15.24cm x 17.15cm); U.S. Patent # 10,058,094